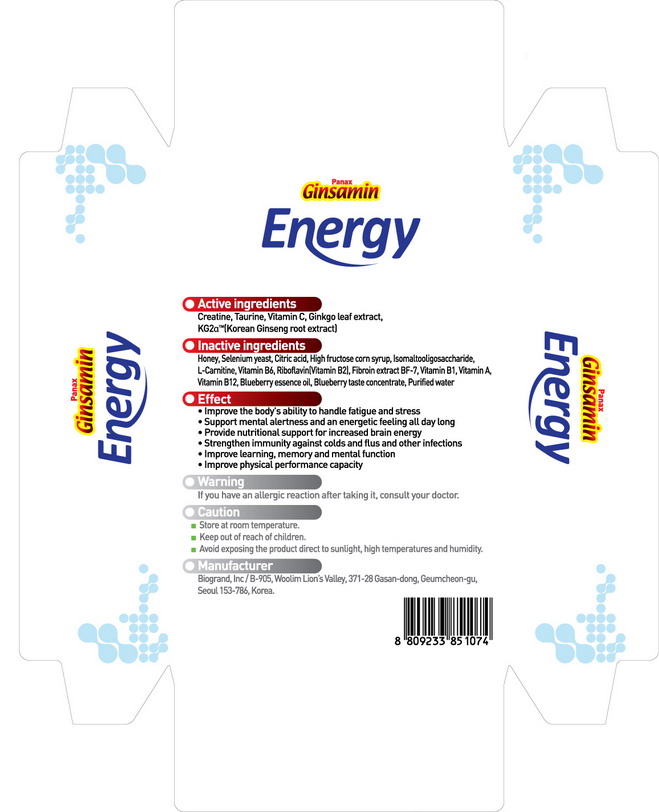 DRUG LABEL: Ginsamin Energy
NDC: 44738-7001 | Form: LIQUID
Manufacturer: Biogrand Co., Ltd
Category: otc | Type: HUMAN OTC DRUG LABEL
Date: 20100307

ACTIVE INGREDIENTS: GINKGO 160 mg/20 g; ASIAN GINSENG 200 mg/20 g; CREATINE 10000 mg/20 g; TAURINE 1000 mg/20 g; ASCORBIC ACID 1000 mg/20 g

Drug Facts

ACTIVE INGREDIENT

Active Ingredients: Ginkgo leaf extract, Korean ginseng root extract, Creatine, Taurine, Vitamin C

DESCRIPTION

Product name
Ginsamin Energy
Active ingredients
Ginkgo leaf extract, Korean ginseng root extract, Creatine, Taurine, Vitamin C
Inactive ingredients
vitamin A, vitamin B1, riboflavin, vitamin B6, vitamin B12, L-cystine, blueberry,
purified water, selenium yeast, honey, citric acid, fructose
Effect
• improve the body's ability to handle fatigue and stress
• support mental alertnss and an energetic feeling all day long
• provide nutritional support for increased brain energy
• strengthen immunity against colds and flus and other infections
• improve learning, memory and mental function
• improve physical performance capacity
Warning
If you have an allergic reaction after taking it, consult your doctor
Caution
• Store at room temperature.
• Keep out of reach of children.
• Avoid exposing the product direct to sunlight, high temperatures and humidity.
• Manufacturer
Manufacturer
Biogrand, lnc / B-905, Woolim Lion’s Valley, 371-28 Gasan-dong, Geumcheon-gu, Seoul 153-786, Korea